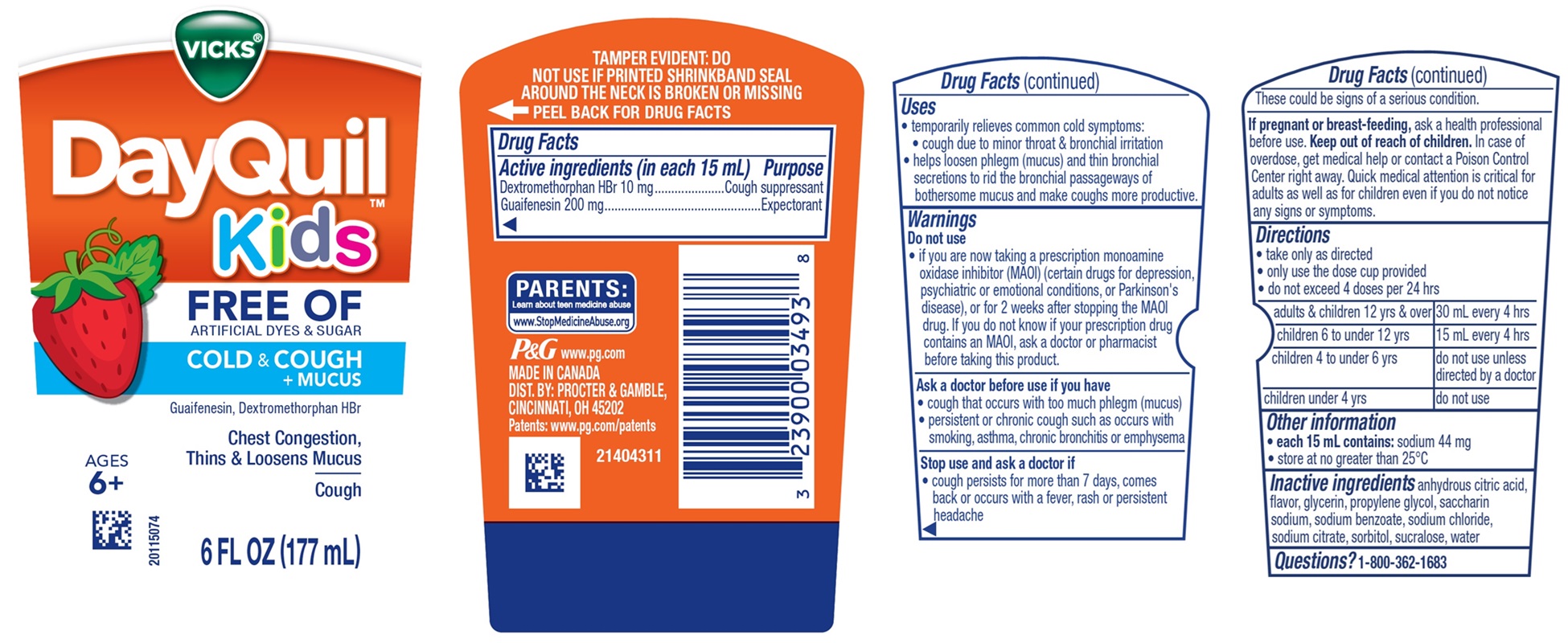 DRUG LABEL: Vicks DayQuil Kids
NDC: 84126-310 | Form: LIQUID
Manufacturer: The Procter & Gamble Manufacturing Company
Category: otc | Type: HUMAN OTC DRUG LABEL
Date: 20251201

ACTIVE INGREDIENTS: DEXTROMETHORPHAN HYDROBROMIDE 10 mg/15 mL; GUAIFENESIN 200 mg/15 mL
INACTIVE INGREDIENTS: SODIUM CHLORIDE; GLYCERIN; SODIUM BENZOATE; SORBITOL; ANHYDROUS CITRIC ACID; PROPYLENE GLYCOL; WATER; SACCHARIN SODIUM; SODIUM CITRATE; SUCRALOSE

VICKS®DayQuil™ Kids FREE OF ARTIFICIAL DYES & SUGAR
COLD & COUGH + MUCUS Liquid

Drug Facts

Active ingredients (in each 15 mL)

Dextromethorphan HBr 10 mg
Guaifenesin 200 mg

Purpose

Cough suppressant
Expectorant

Uses

- temporarily relieves common cold symptoms:
- cough due to minor throat & bronchial irritation
- helps loosen phlegm (mucus) and thin bronchial secretions to rid the bronchial passageways of bothersome mucus and make coughs more productive.

Warnings

Do not use

- if you are now taking a prescription monoamine oxidase inhibitor (MAOI) (certain drugs for depression, psychiatric or emotional conditions, or Parkinson's disease), or for 2 weeks after stopping the MAOI drug. If you do not know if your prescription drug contains an MAOI, ask a doctor or pharmacist before taking this product.

Ask a doctor before use if you have

- cough that occurs with too much phlegm (mucus)
- persistent or chronic cough such as occurs with smoking, asthma, chronic bronchitis or emphysema

Stop use and ask a doctor if

- cough persists for more than 7 days, comes back or occurs with a fever, rash or persistent headache

These could be signs of a serious condition.

If pregnant or breast-feeding,

ask a health professional before use.

Keep out of reach of children.

OVERDOSAGE

In case of overdose, get medical help or contact a Poison Control Center right away. Quick medical attention is critical for adults as well as for children even if you do not notice any signs or symptoms.

Directions

- take only as directed
- only use the dose cup provided
- do not exceed 4 doses per 24 hrs

adults & children 12 yrs & over | 30 mL every 4 hrs
children 6 to under 12 yrs | 15 mL every 4 hrs
children 4 to under 6 yrs | do not use unless directed by doctor
children under 4 yrs | do not use

Other information

- each 15 mL contains:sodium 44 mg
- store at no greater than 25°C

Inactive ingredients

anhydrous citric acid, flavor, glycerin, propylene glycol, saccharin sodium, sodium benzoate, sodium chloride, sodium citrate, sorbitol, sucralose, water

Questions?

1-800-362-1683

TAMPER EVIDENT: DO NOT USE IF PRINTED SHRINKBAND SEAL AROUND THE NECK IS BROKEN OR MISSING

MADE IN CANADA

DIST. BY: PROCTER & GAMBLE, CINCINNATI, OH 45202

PRINCIPAL DISPLAY PANEL - 177 ml Bottle Label

VICKS®

DayQuil™

Kids

FREE OF

ARTIFICIAL DYES & SUGAR

COLD & COUGH + MUCUS

Guaifenesin, Dextromethorphan HBr

Chest Congestion,

Thins & Loosens Mucus

Cough

AGES 6+

6 FL OZ (177 mL)